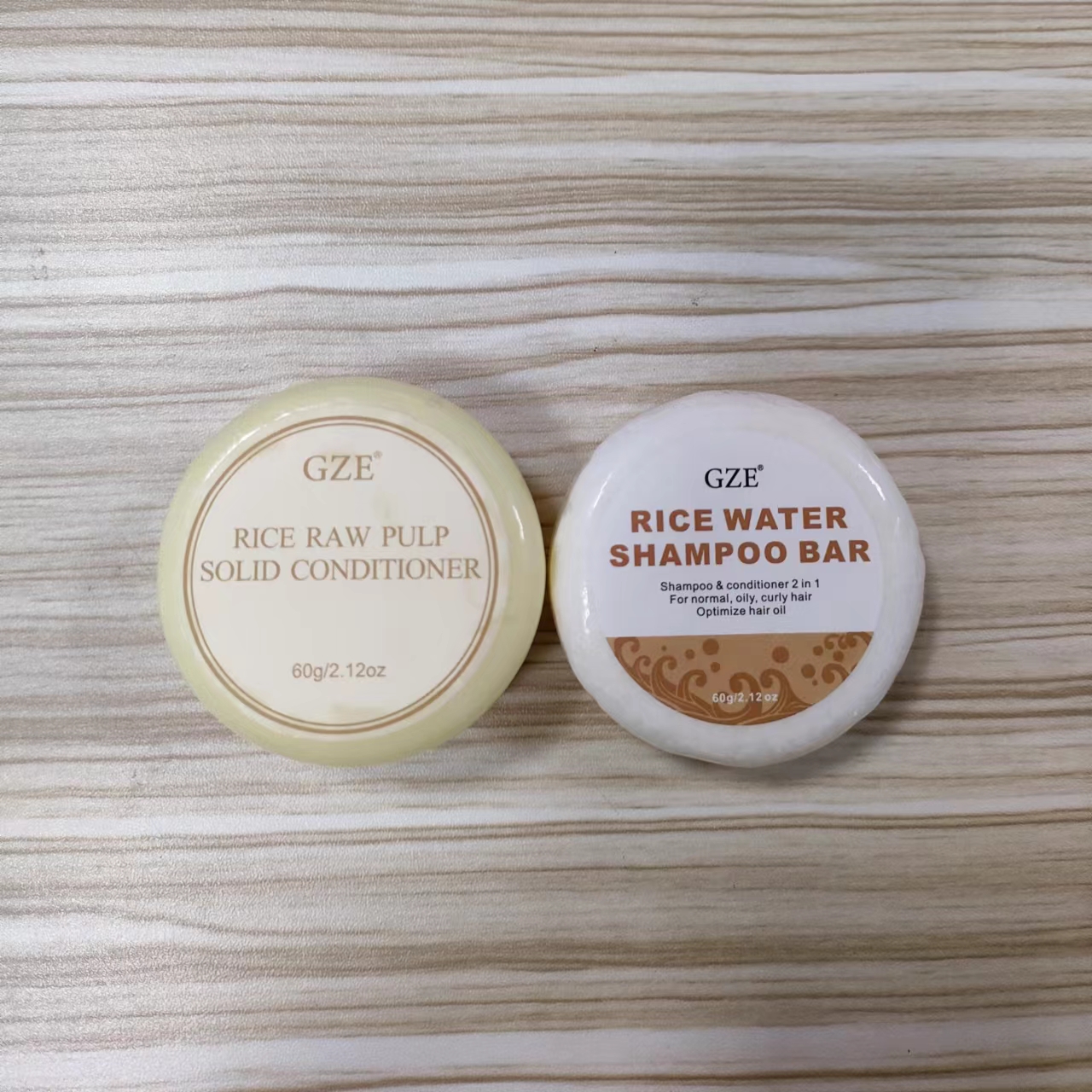 DRUG LABEL: GZE Rice Water ShampooConditioner Bar
NDC: 74458-290 | Form: SOAP
Manufacturer: Guangzhou Yilong Cosmetics Co., Ltd
Category: otc | Type: HUMAN OTC DRUG LABEL
Date: 20241007

ACTIVE INGREDIENTS: RICE BRAN OIL 12.5 g/100 g
INACTIVE INGREDIENTS: COCONUT OIL; SODIUM COCOYL ISETHIONATE; OLIVE OIL; LIMOSILACTOBACILLUS FERMENTUM; ORYZA SATIVA WHOLE; ARGAN OIL; TOCOPHEROL

GZE Rice Water ShampooConditioner Bar

ACTIVE INGREDIENT

RICE BRAN OIL 12.5%

INACTIVE INGREDIENT

COCONUT OIL
SODIUM COCOYLISETHIONATE
OLIE OIL
LIMOSILACTOBACILLUS FERMENTUM
ORYZA SATIVA WHOLE
ARGAN OIL
TOCOPHEROL

INDICATIONS AND USAGE

Shampoo BAr: Wet hair, dip some water on the soap, rub soap with your hands or foaming net to make a dense foam.Apply the foam on hair, gently massage scalp for 3.5 minutes, rinse with water,

Conditioner Bar:After shampooing, wet the conditioner bar and slide down your hair5 -6 times.Massage the goodness into your hair and leave for 1-2 minutes.Rinse thoroughly for soft hair.

PURPOSE

Cleanses and cares for scalp and hair.

WARNINGS

For external use only.

Stop use and ask a doctor if rash occurs.

Do not use on damaged or broken skin.

When using this product keep out of eyes. Rinse with water to remove.

Keep out of reach of children. If swallowed, get medical help or contact a Poison Control Center right away.

DOSAGE AND ADMINISTRATION

Shampoo BAr: Wet hair, dip some water on the soap, rub soap with your hands or foaming net to make a dense foam.Apply the foam on hair, gently massage scalp for 3.5 minutes, rinse with water,

Conditioner Bar:After shampooing, wet the conditioner bar and slide down your hair5 -6 times.Massage the goodness into your hair and leave for 1-2 minutes.Rinse thoroughly for soft hair.